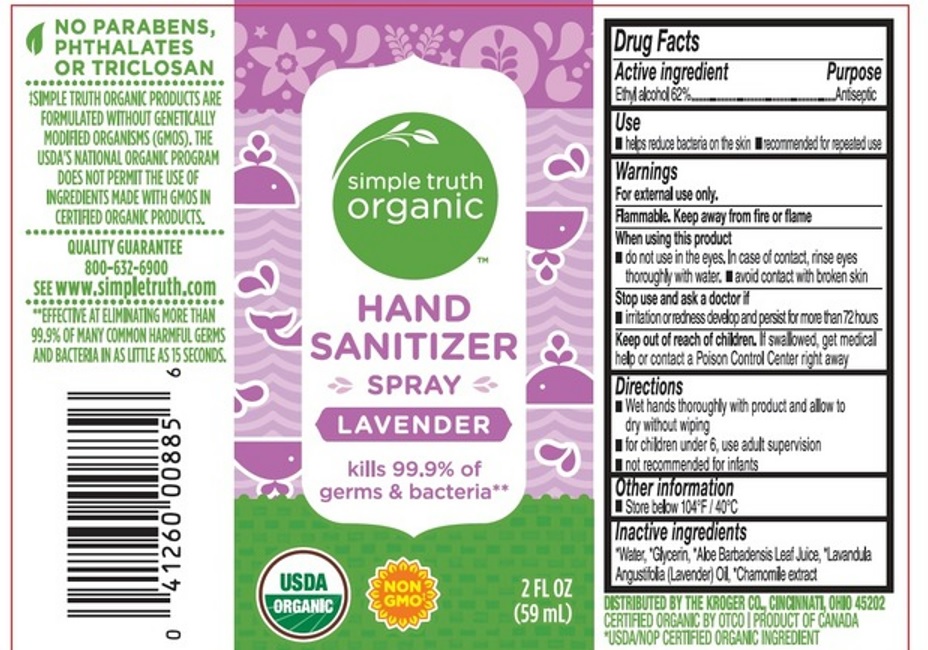 DRUG LABEL: Simple Truth Organic Hand Sanitizer Lavender
NDC: 82561-001 | Form: SPRAY
Manufacturer: Vital Innovations Inc.
Category: otc | Type: HUMAN OTC DRUG LABEL
Date: 20220420

ACTIVE INGREDIENTS: ALCOHOL 62 mL/100 mL
INACTIVE INGREDIENTS: ALOE VERA LEAF; GLYCERIN; WATER; LAVENDER OIL; CHAMOMILE

Simple Truth Organic Hand Sanitizer Spray Lavender

Active ingredient

Ethyl alcohol 62%

Purpose

Antiseptic

Use

- helps reduce bacteria on the skin
- recommended for repeated use

Warnings

For external use only.

Flammable. Keep away from fire or flame.

When using this product

- do not use in the eyes. In case of contact, rinse eyes thoroughly with water
- avoid contact with broken skin

Stop use and ask a doctor if

- irritation or redness develop and persist for more than 72 hours

Keep out of reach of children.

If swallowed, get medical help or contact a Poison Control Center right away.

Directions

- Wet hands thoroughly with product and allow to dry without wiping
- for children under 6, use adult supervision
- not recommended for infants

Other information

- Store below 104ºF / 40ºC

Inactive ingredients

*Water, *Glycerin, *Aloe Barbadensis Leaf Juice, *Lavandula Angustifolia (Lavender) Oil, *Chamomile extract

*USDA/NOP CERTIFIED ORGANIC INGREDIENT

Company Information

DISTRIBUTED BY THE KROGER CO., CINCINNATI, OHIO 45202

CERTIFIED ORGANIC BY OTCO

PRODUCT OF CANADA